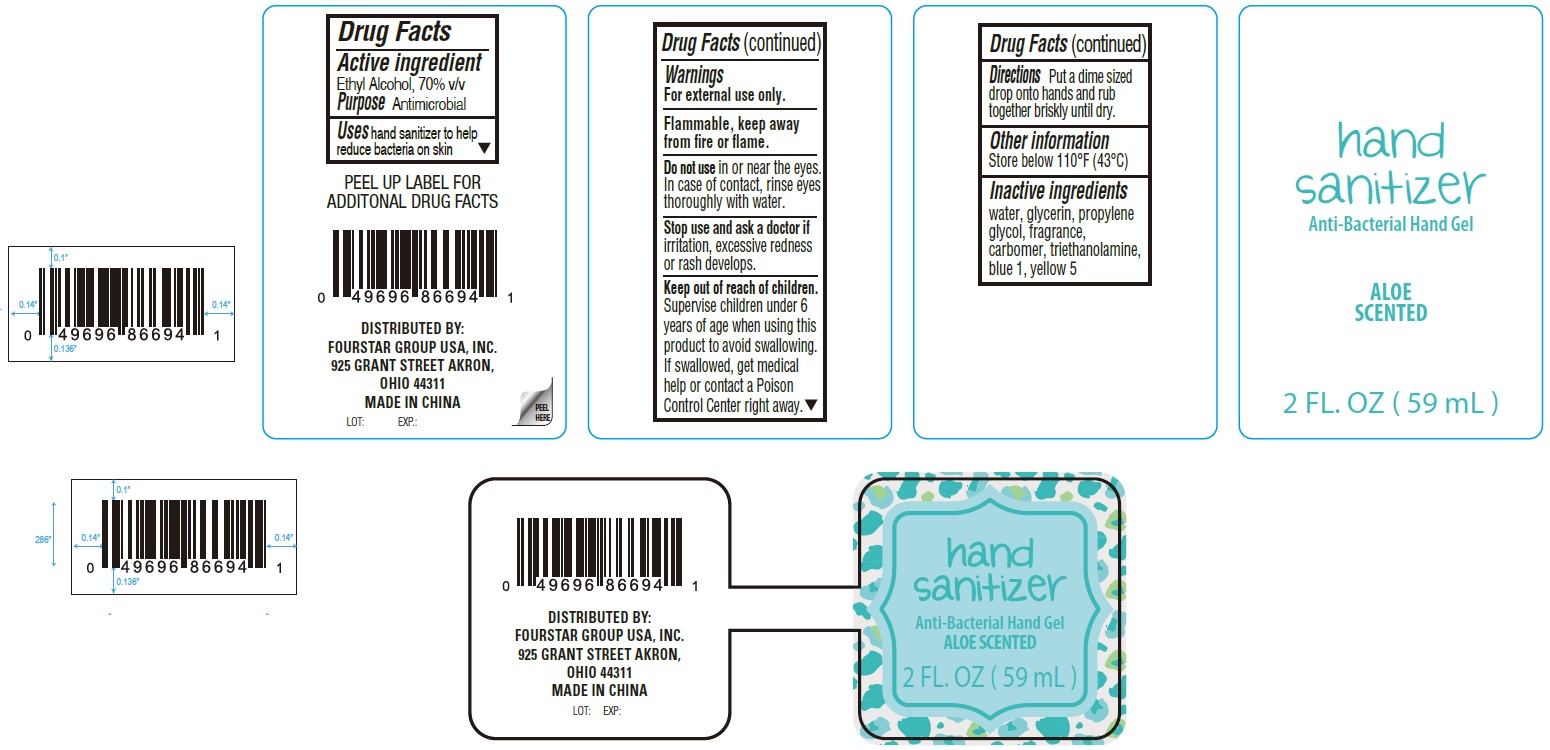 DRUG LABEL: Aloe scented anti-bacterial hand sanitizer
NDC: 80684-034 | Form: GEL
Manufacturer: FOURSTAR GROUP USA, INC.
Category: otc | Type: HUMAN OTC DRUG LABEL
Date: 20231026

ACTIVE INGREDIENTS: ALCOHOL 70 mL/100 mL
INACTIVE INGREDIENTS: CARBOMER HOMOPOLYMER, UNSPECIFIED TYPE; TROLAMINE; FD&C BLUE NO. 1; FD&C YELLOW NO. 5; WATER; GLYCERIN; PROPYLENE GLYCOL

Aloe scented anti-bacterial hand sanitizer Gel

Active ingredient

Ethyl Alcohol, 70% v/v

Purpose

Antimicrobial

Uses

hand sanitizer to help reduce bacteria on skin

Warnings

For external use only.

Flammable, keep away from fire or flame.

Do not use

in or near the eyes. In case of contact, rinse eyes thoroughly with water.

Stop use and ask a doctor if

irritation, excessive redness or rash develops.

Keep out of reach of children.

Supervise children under 6 years of age when using this product to avoid swallowing. If swallowed, get medical help or contact a Poison Control Center right away.

Directions

Put a dime sized drop onto hands and rub together briskly until dry.

Other information

Store below 110°F (43°C)

Inactive ingredients

water, glycerin, propylene glycol, fragrance, carbomer, triethanolamine, blue 1, yellow 5